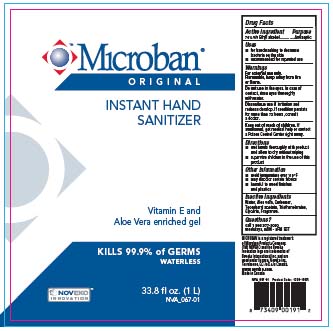 DRUG LABEL: Microban
NDC: 49955-600 | Form: GEL
Manufacturer: Noveko Inc
Category: otc | Type: HUMAN OTC DRUG LABEL
Date: 20100126

ACTIVE INGREDIENTS: ALCOHOL 0.7 L/1 L
INACTIVE INGREDIENTS: WATER; ALOE VERA LEAF; .ALPHA.-TOCOPHEROL ACETATE, D-; TROLAMINE; GLYCERIN

Active ingredient Purpose

70% V/V Ethyl alcohol.....Antiseptic

Uses

for handwashing to decrease bacteria on the skin

recommended for repeated use

Warnings

For external use only.

Flammable, keep away from fire or flame.

Do not use in the eyes. In case of

contact, rinse eyes thoroughly

with water.

Discontinue use if irritation and

redness develop.

ASK DOCTOR

If condition persists

for more than 72 hours, consult

a doctor.

Keep out of reach of children. If

swallowed, get medical help or contact

a Poison Control Center right away.

Directions

wet hands thoroughly with product

and allow to dry without wiping

supervise children in the use of this product

Other Information

avoid temperature over 110F

may discolor certain fabrics

harmful to wood finishes and plastics

Inactive ingredients

Water, Aloe vera, Carbomer, Tocopheryl acetate, Triethanolamine,

Glycerin, Fragrance.

Questions?

call 1 866 377-3030

weekdays, 9AM - 5PM EST

Enter section text here

PACKAGE LABEL

ANTISEPTIC HAND SANITIZER

Microban

ORIGINAL
KILLS 99.9% OF GERMS

WATERLESS

Vitamin E and Aloe Vera enriched gel.

fl oz. (L/mL)